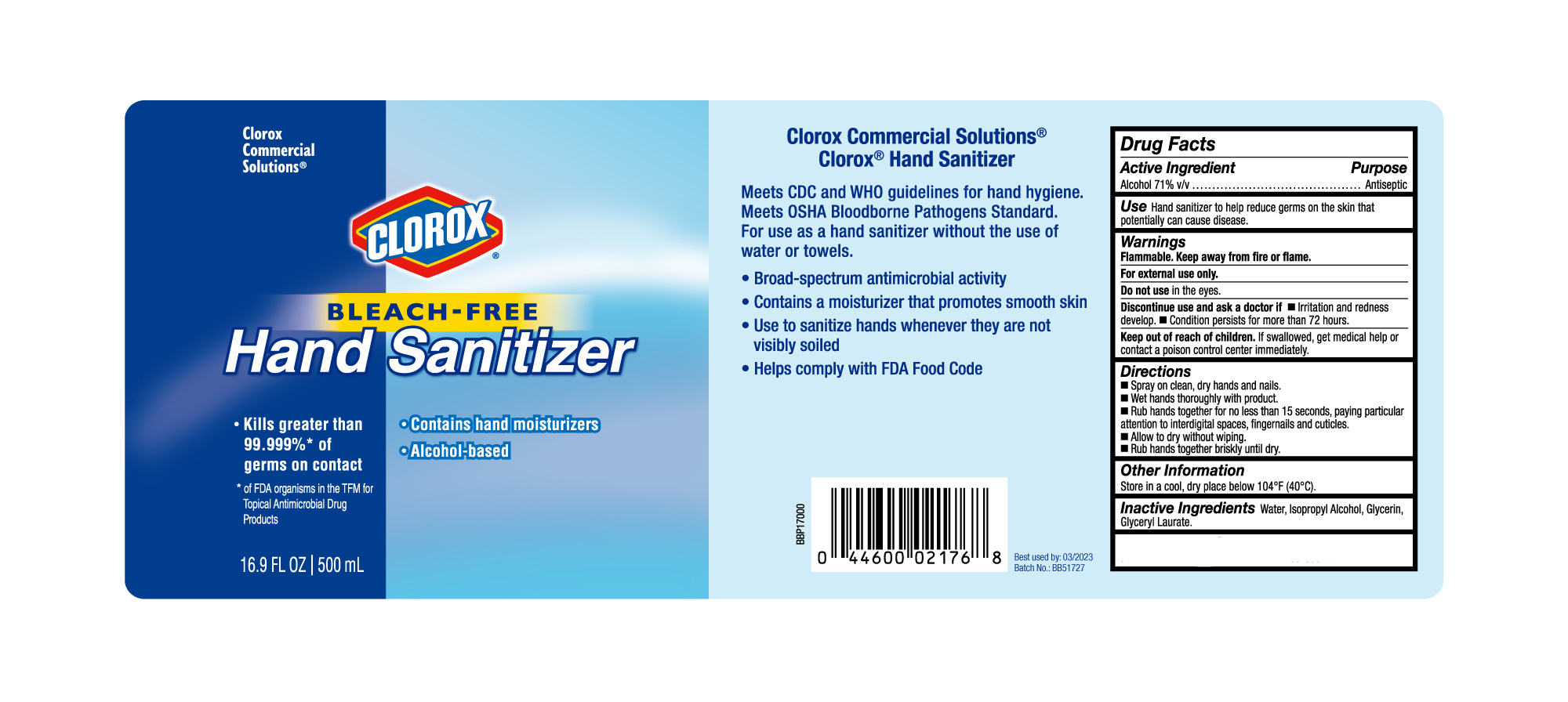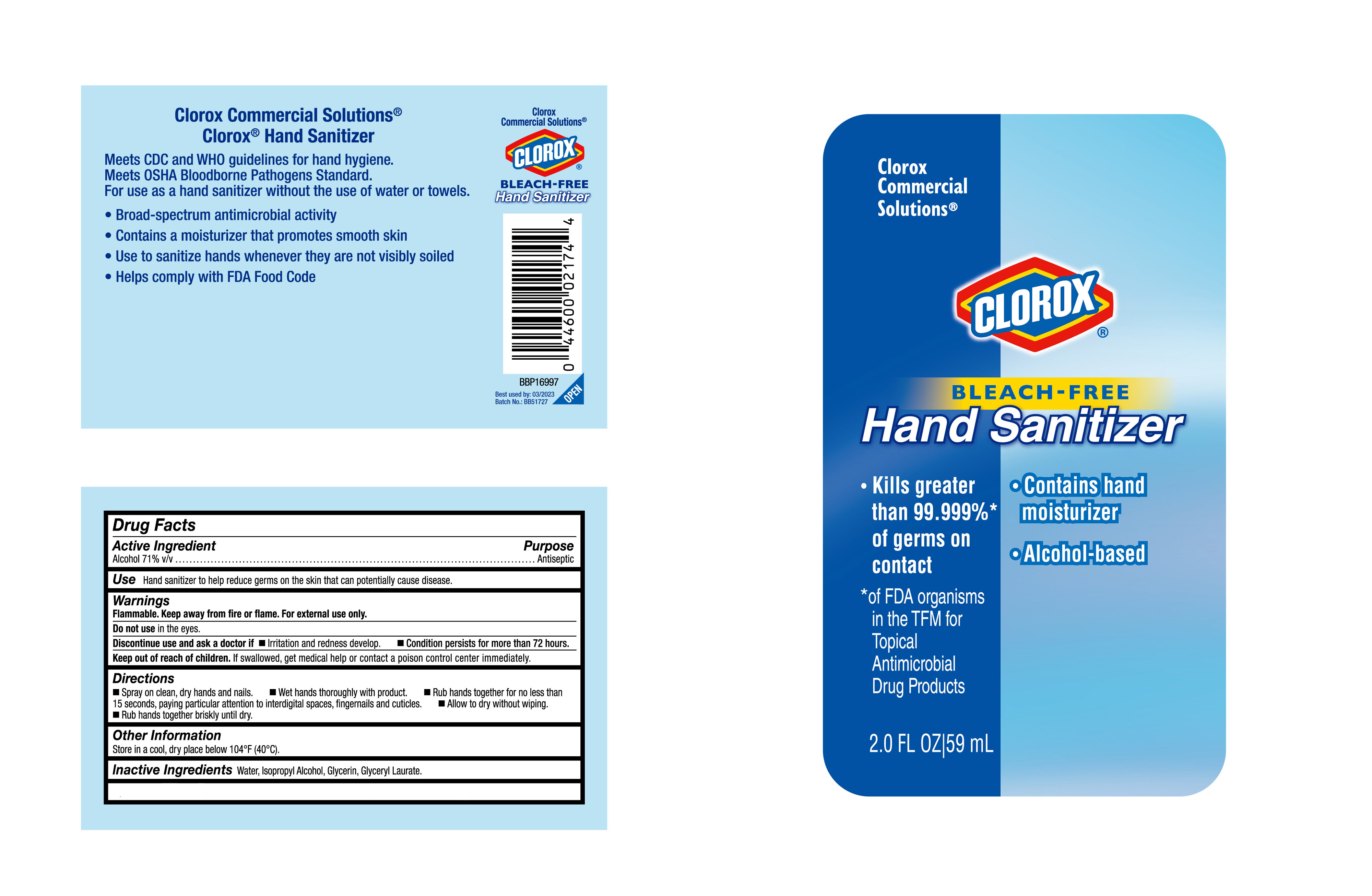 DRUG LABEL: HAND SANITIZER
NDC: 47993-329 | Form: GEL
Manufacturer: INGBO JIANGBEI OCEAN STAR TRADING CO.,LTD
Category: otc | Type: HUMAN OTC DRUG LABEL
Date: 20210617

ACTIVE INGREDIENTS: ALCOHOL 71 mL/100 mL
INACTIVE INGREDIENTS: WATER; ISOPROPYL ALCOHOL; GLYCERIN; GLYCERYL LAURATE

47993-329

Active ingredients

Alcohol 71% v/v

PURPOSE

Antiseptic

Uses：

Hand sanitizer to help reduce germs on the skin that potentially can cause disease.

Warnings:

Flammable. Keep away from fire or flame

For external use only.

Discontinue use and ask a doctor if

- Irritation and redness develop.
- Condition persists for more than 72 hours.

Keep out of reach of children. If swallowed, get medical help or contact a poison control center immediately.

Directions:

- Spray on clean, dry hands and nails.
- Wet hands thoroughly with product.
- Rub hands together for no less than 15 seconds, paying particular attention to interdigital spaces, fingernails and cuticles.
- Allow to dry without wiping.
- Rub hands together briskly until dry.

Other information:

Store in a cool, dry place below 104℉ (40℃).

Inactive ingredients:

Water, Isopropyl Alcohol, Glycerin, Glyceryl Laurate.